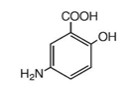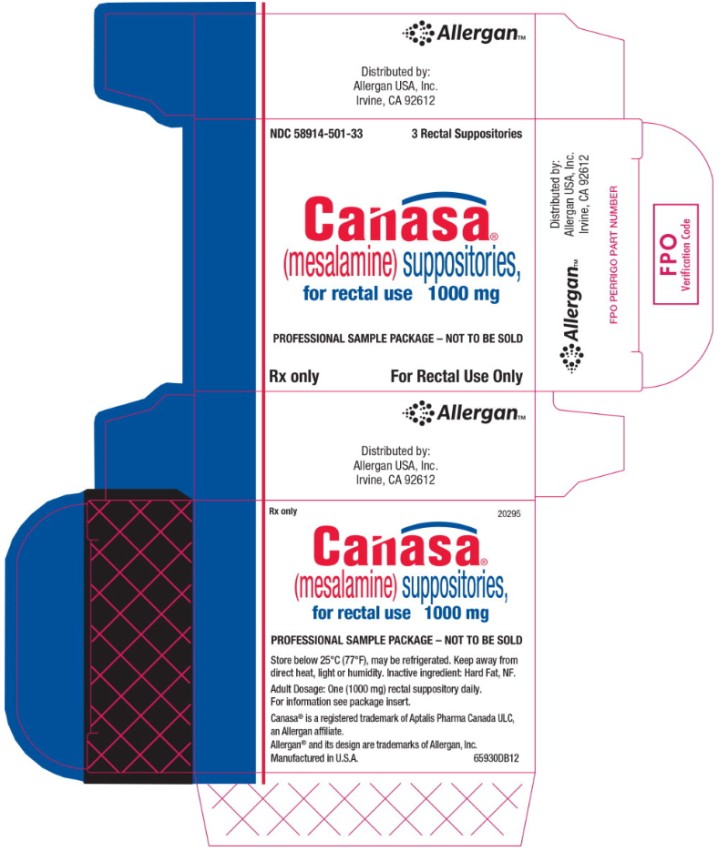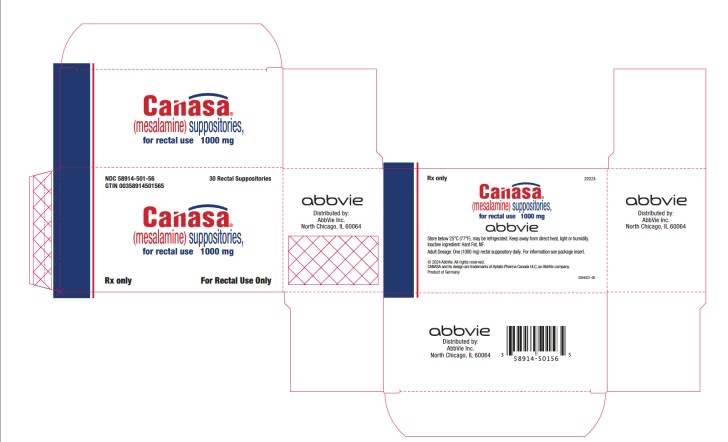 DRUG LABEL: Canasa
NDC: 58914-501 | Form: SUPPOSITORY
Manufacturer: Allergan, Inc.
Category: prescription | Type: HUMAN PRESCRIPTION DRUG LABEL
Date: 20240908

ACTIVE INGREDIENTS: MESALAMINE 1000 mg/1 1
INACTIVE INGREDIENTS: FAT, HARD

HIGHLIGHTS OF PRESCRIBING INFORMATION

These highlights do not include all the information needed to use CANASA safely and effectively. See full prescribing information for CANASA.
CANASA® (mesalamine) suppositories, for rectal use
Initial U.S. Approval: 1987

1 INDICATIONS AND USAGE

CANASA is an aminosalicylate indicated in adults for the treatment of mildly to moderately active ulcerative proctitis. (1)

2 DOSAGE AND ADMINISTRATION

Dosage

The recommended adult dosage is 1000 mg administered rectally once daily at bedtime for 3 to 6 weeks. Safety and effectiveness beyond 6 weeks have not been established. (2)

Administration Instructions:

- Evaluate renal function prior to initiation of CANASA and periodically while on therapy. (2, 5.1)
- Do not cut or break the suppository. (2)
- Drink an adequate amount of fluids. (2, 5.7)
- Retain the suppository for one to three hours or longer, if possible. (2)
- CANASA suppositories will cause staining of direct contact surfaces, including but not limited to fabrics, flooring, painted surfaces, marble, granite, vinyl, and enamel. Keep CANASA away from these surfaces to prevent staining. (2)

3 DOSAGE FORMS AND STRENGTHS

Suppository: 1000 mg (3)

4 CONTRAINDICATIONS

Known or suspected hypersensitivity to salicylates or aminosalicylates or to any ingredients in the formulation. (4, 5.3)

5 WARNINGS AND PRECAUTIONS

- Renal Impairment: Evaluate the risks and benefits in patients with known renal impairment or taking nephrotoxic drugs; monitor renal function. Discontinue CANASA if renal function deteriorates. (5.1, 7.1, 8.6)
- Mesalamine-Induced Acute Intolerance Syndrome: Symptoms may be difficult to distinguish from an exacerbation of ulcerative colitis; monitor for worsening symptoms; discontinue treatment if acute intolerance syndrome is suspected. (5.2)
- Hypersensitivity Reactions, including Myocarditis and Pericarditis: Evaluate patients immediately and discontinue if a hypersensitivity reaction is suspected. (5.3)
- Hepatic Failure: Evaluate the risks and benefits in patients with known liver impairment. (5.4)
- Severe Cutaneous Adverse Reactions: Discontinue at the first signs or symptoms of severe cutaneous adverse reactions or other signs of hypersensitivity and consider further evaluation. (5.5)
- Photosensitivity: Advise patients with pre-existing skin conditions to avoid sun exposure, wear protective clothing, and use a broad-spectrum sunscreen when outdoors. (5.6)
- Nephrolithiasis: Mesalamine-containing stones are undetectable by standard radiography or computed tomography (CT). Ensure adequate hydration during treatment. (5.7)
- Interaction with Laboratory Test for Urinary Normetanephrine: Spuriously elevated test results may occur with liquid chromatography with electrochemical detection in patients receiving CANASA; use alternative, selective assay for normetanephrine. (5.8)

6 ADVERSE REACTIONS

The most common adverse reactions (≥ 1%) are: dizziness, rectal pain, fever, rash, acne and colitis. (6.1)

To report SUSPECTED ADVERSE REACTIONS, contact AbbVie at 1-800-678-1605 or FDA at 1-800-FDA-1088 or www.fda.gov/medwatch

7 DRUG INTERACTIONS

- Nephrotoxic Agents including NSAIDs: Increased risk of nephrotoxicity; monitor for changes in renal function and mesalamine-related adverse reactions. (7.1)
- Azathioprine or 6-Mercaptopurine: Increased risk of blood disorders; monitor complete blood cell counts and platelet counts. (7.2)

8 USE IN SPECIFIC POPULATIONS

Geriatric Patients: Increased risk of blood dyscrasias; monitor complete blood cell counts and platelet counts. (8.5)

FULL PRESCRIBING INFORMATION

1 INDICATIONS AND USAGE

CANASA is indicated in adults for the treatment of mildly to moderately active ulcerative proctitis.

2 DOSAGE AND ADMINISTRATION

Dosage

The recommended dosage of CANASA in adults is 1000 mg administered rectally once daily at bedtime for 3 to 6 weeks depending on symptoms and sigmoidoscopic findings. Safety and effectiveness of CANASA beyond 6 weeks have not been established.

Administration Instructions:

- Evaluate renal function prior to initiation of CANASA therapy [see Warnings and Precautions (5.1)].
- Do not cut or break the suppository.
- Retain the suppository for one to three hours or longer, if possible.
- Drink an adequate amount of fluids [see Warnings and Precautions (5.7)]
- If a dose of CANASA is missed, administer as soon as possible, unless it is almost time for next dose. Do not use two CANASA suppositories at the same time to make up for a missed dose.
- CANASA suppositories will cause staining of direct contact surfaces, including but not limited to fabrics, flooring, painted surfaces, marble, granite, vinyl, and enamel. Keep CANASA away from these surfaces to prevent staining.

3 DOSAGE FORMS AND STRENGTHS

CANASA Suppository: 1000 mg mesalamine in a bullet shaped, light tan to grey suppository.

4 CONTRAINDICATIONS

CANASA is contraindicated in patients with known or suspected hypersensitivity to salicylates or aminosalicylates or to any ingredients in the suppository vehicle [see Warnings and Precautions (5.3), Adverse Reactions (6.2), and Description (11)].

5 WARNINGS AND PRECAUTIONS

5.1 Renal Impairment

Renal impairment, including minimal change disease, acute and chronic interstitial nephritis, and renal failure, has been reported in patients given products such as CANASA that contain mesalamine or are converted to mesalamine. In animal studies, the kidney was the principal organ of mesalamine toxicity [see Adverse Reactions (6.2), Nonclinical Toxicology (13.2)].

Evaluate renal function prior to initiation of CANASA and periodically while on therapy.

Evaluate the risks and benefits of using CANASA in patients with known renal impairment or a history of renal disease or taking concomitant nephrotoxic drugs. Discontinue CANASA if renal function deteriorates while on therapy [see Drug Interactions (7.1), Use in Specific Populations (8.6)].

5.2 Mesalamine-Induced Acute Intolerance Syndrome

Mesalamine has been associated with an acute intolerance syndrome that may be difficult to distinguish from an exacerbation of ulcerative colitis. Although the exact frequency of occurrence has not been determined, it has occurred in 3% of patients in controlled clinical trials of mesalamine or sulfasalazine. Symptoms include cramping, acute abdominal pain and bloody diarrhea, and sometimes fever, headache, malaise, pruritus, conjunctivitis, and rash. Monitor patients for worsening of these symptoms while on treatment. If acute intolerance syndrome is suspected, promptly discontinue treatment with CANASA.

5.3 Hypersensitivity Reactions

Hypersensitivity reactions have been reported in patients taking sulfasalazine. Some patients may have a similar reaction to CANASA or to other compounds that contain or are converted to mesalamine.

As with sulfasalazine, mesalamine-induced hypersensitivity reactions may present as internal organ involvement, including myocarditis, pericarditis, nephritis, hepatitis, pneumonitis and hematologic abnormalities. Evaluate patients immediately if signs or symptoms of a hypersensitivity reaction are present. Discontinue CANASA if an alternative etiology for the signs and symptoms cannot be established.

5.4 Hepatic Failure

There have been reports of hepatic failure in patients with pre-existing liver disease who have been administered other products containing mesalamine. Evaluate the risks and benefits of using CANASA in patients with known liver impairment.

5.5 Severe Cutaneous Adverse Reactions

Severe cutaneous adverse reactions, including Stevens-Johnson syndrome (SJS) and toxic epidermal necrolysis (TEN), drug reaction with eosinophilia and systemic symptoms (DRESS), and acute generalized exanthematous pustulosis (AGEP) have been reported in association with the use of mesalamine [see Adverse Reactions (6.2)]. Discontinue CANASA at the first signs or symptoms of severe cutaneous adverse reactions or other signs of hypersensitivity and consider further evaluation.

5.6 Photosensitivity

In patients treated with mesalamine or sulfasalazine who have pre-existing skin conditions such as atopic dermatitis and atopic eczema have reported more severe photosensitivity reactions. Advise patients to avoid sun exposure, wear protective clothing, and use a broad-spectrum sunscreen when outdoors.

5.7 Nephrolithiasis

Cases of nephrolithiasis have been reported with the use of mesalamine, including stones of 100% mesalamine content. Mesalamine-containing stones are radiotransparent and undetectable by standard radiography or computed tomography (CT). Ensure adequate hydration during treatment with CANASA.

5.8 Interaction with Laboratory Test for Urinary Normetanephrine

Use of mesalamine may lead to spuriously elevated test results when measuring urinary normetanephrine by liquid chromatography with electrochemical detection, because of the similarity in the chromatograms of normetanephrine and mesalamine's main metabolite, N-acetylaminosalicylic acid. Consider an alternative, selective assay for normetanephrine.

6 ADVERSE REACTIONS

The following serious or clinically significant adverse reactions are described elsewhere in labeling:

- Renal Impairment [see Warnings and Precautions (5.1)]
- Mesalamine-Induced Acute Intolerance Syndrome [see Warnings and Precautions (5.2)]
- Hypersensitivity Reactions [see Warnings and Precautions (5.3)]
- Hepatic Failure [see Warnings and Precautions (5.4)]
- Severe Cutaneous Adverse Reactions [see Warnings and Precautions (5.5)]
- Photosensitivity [see Warnings and Precautions (5.6)]
- Nephrolithiasis [see Warnings and Precautions (5.7)]

6.1 Clinical Trials Experience

Because clinical trials are conducted under widely varying conditions, adverse reaction rates observed in the clinical trials of a drug cannot be directly compared to rates in the clinical trials of another drug and may not reflect the rates observed in practice.

The most common adverse reactions in adult patients with mildly to moderately active ulcerative proctitis in double-blind, placebo-controlled trials are summarized in the Table 1 below.

Table 1: Adverse Reactions Occurring in More Than 1% of Mesalamine Suppository Treated Patients (Comparison to Placebo)
Symptom | Mesalamine (n = 177) |  | Placebo (n = 84)
 | N | % | N | %
Dizziness | 5 | 3 | 2 | 2.4
Rectal Pain | 3 | 1.8 | 0 | 0
Fever | 2 | 1.2 | 0 | 0
Rash | 2 | 1.2 | 0 | 0
Acne | 2 | 1.2 | 0 | 0
Colitis | 2 | 1.2 | 0 | 0

In a multicenter, open-label, randomized, parallel group study in 99 patients comparing the CANASA 1000 mg suppository administered nightly to that of the mesalamine 500 mg suppository twice daily. The most common adverse reactions in both groups were headache (14%), flatulence (5%), abdominal pain (5%), diarrhea (3%), and nausea (3%). Three (3) patients discontinued medication because of an adverse reaction; one of these adverse reactions (headache) was deemed possibly related to study medication. The recommended dosage of CANASA is 1000 mg administered rectally once daily at bedtime [see Dosage and Administration (2)].

6.2 Postmarketing Experience

The following adverse reactions have been identified during post-approval use of CANASA or other mesalamine-containing products. Because these reactions are reported voluntarily from a population of uncertain size, it is not always possible to reliably estimate their frequency or establish a causal relationship to drug exposure.

- Body as a Whole: drug fever, fatigue, lupus-like syndrome, medication residue
- Cardiac Disorders: myocarditis, pericarditis, pericardial effusion [see Warnings and Precautions (5.3)]
- Endocrine: Nephrogenic diabetes insipidus
- Eye disorders: eye swelling
- Gastrointestinal Disorders: abdominal cramps, abdominal distension, anal pruritus, anorectal discomfort, constipation, feces discolored, flatulence, frequent bowel movements, gastrointestinal bleeding, mucus stools, nausea, painful defecation, pancreatitis, proctalgia, rectal discharge, rectal tenesmus, stomach discomfort, vomiting
- Hepatic Disorders: cholestatic jaundice, hepatitis, jaundice, Kawasaki-like syndrome including changes in liver enzymes, liver necrosis, liver failure
- Hematologic Disorders: agranulocytosis, aplastic anemia, thrombocytopenia
- Neurological/Psychiatric Disorders: Guillain-Barre syndrome, peripheral neuropathy, transverse myelitis, intracranial hypertension
- Renal Disorders: interstitial nephritis, renal failure, minimal change disease, nephrolithiasis [see Warnings and Precautions (5.1, 5.7)]
  ○ Urine discoloration occurring ex-vivo caused by contact of mesalamine, including inactive metabolite, with surfaces or water treated with hypochlorite containing bleach
- Respiratory, Thoracic and Mediastinal Disorders: hypersensitivity pneumonitis (including allergic alveolitis, eosinophilic pneumonitis, interstitial pneumonitis), pleuritis/pleurisy
- Skin and Subcutaneous Tissue Disorder: alopecia, erythema, erythema nodosum, pruritus, psoriasis, pyoderma gangrenosum, urticaria, SJS/TEN, DRESS and AGEP [see Warnings and Precautions (5.5)]
- Urogenital: reversible oligospermia

7 DRUG INTERACTIONS

7.1 Nephrotoxic Agents, Including Non-Steroidal Anti-Inflammatory Drugs

The concurrent use of mesalamine with known nephrotoxic agents, including nonsteroidal anti-inflammatory drugs (NSAIDs) may increase the risk of nephrotoxicity. Monitor patients taking nephrotoxic drugs for changes in renal function and mesalamine-related adverse reactions [see Warnings and Precautions (5.1)].

7.2 Azathioprine or 6-Mercaptopurine

The concurrent use of mesalamine with azathioprine or 6-mercaptopurine and/or other drugs known to cause myelotoxicity may increase the risk for blood disorders, bone marrow failure, and associated complications. If concomitant use of CANASA and azathioprine or 6-mercaptopurine cannot be avoided, monitor blood tests, including complete blood cell counts and platelet counts.

7.3 Interference With Urinary Normetanephrine Measurements

Use of mesalamine may lead to spuriously elevated test results when measuring urinary normetanephrine by liquid chromatography with electrochemical detection, because of the similarity in the chromatograms of normetanephrine and mesalamine's main metabolite, N-acetylaminosalicylic acid. Consider an alternative, selective assay for normetanephrine [see Warnings and Precautions (5.8)].

8 USE IN SPECIFIC POPULATIONS

8.1 Pregnancy

Risk Summary

Limited published data on mesalamine use in pregnant women are insufficient to inform a drug-associated risk. No evidence of teratogenicity was observed in rats or rabbits when treated during gestation with orally administered mesalamine at doses greater than the recommended human intra-rectal dose (see Data).

The estimated background risk of major birth defects and miscarriage for the indicated populations is unknown. Adverse outcomes in pregnancy occur regardless of the health of the mother or the use of medications. In the U.S. general population, the estimated background risk of major birth defects and miscarriage in clinically recognized pregnancies is 2 to 4% and 15 to 20%, respectively.

Data

Animal Data

Reproduction studies have been performed in rats at oral doses up to 320 mg/kg/day (about 1.7 times the recommended human intra-rectal dose of CANASA, based on body surface area) and in rabbits at oral doses up to 495 mg/kg/day (about 5.4 times the recommended human intra-rectal dose of CANASA, based on body surface area) following administration during the period of organogenesis, and have revealed no evidence of impaired fertility or harm to the fetus due to mesalamine.

8.2 Lactation

Risk Summary

Mesalamine and its N-acetyl metabolite are present in human milk in undetectable to small amounts (see Data). There are limited reports of diarrhea in breastfed infants. There is no information on the effects of the drug on milk production. The lack of clinical data during lactation precludes a clear determination of the risk of CANASA to an infant during lactation; therefore, the developmental and health benefits of breastfeeding should be considered along with the mother’s clinical need for CANASA and any potential adverse effects on the breastfed child from CANASA or from the underlying maternal conditions.

Clinical Considerations

Monitor breastfed infants for diarrhea.

Data

In published lactation studies, maternal mesalamine doses from various oral and rectal formulations and products ranged from 500 mg to 3 g daily. The concentration of mesalamine in milk ranged from non-detectable to 0.11 mg/L. The concentration of the N-acetyl-5-aminosalicylic acid metabolite ranged from 5 to 18.1 mg/L. Based on these concentrations, estimated infant daily dosages for an exclusively breastfed infant are 0 to 0.017 mg/kg/day of mesalamine and 0.75 to 2.72 mg/kg/day of N-acetyl-5-aminosalicylic acid.

8.4 Pediatric Use

The safety and effectiveness of CANASA in pediatric patients for the treatment of mildly to moderately active ulcerative proctitis have not been established. CANASA was evaluated for the treatment of ulcerative proctitis in a 6-week, open-label, single-arm study in 49 patients 5 to 17 years of age, which only included 14 patients with histologically-confirmed cases of ulcerative proctitis. However, efficacy was not demonstrated. Adverse reactions seen in pediatric patients in this trial (abdominal pain, headache, pyrexia, pharyngolaryngeal pain, diarrhea and vomiting) were similar to those seen in adult patients.

8.5 Geriatric Use

Clinical trials of CANASA did not include sufficient numbers of patients aged 65 years and over to determine whether they respond differently from younger patients. Reports from uncontrolled clinical studies and postmarketing reporting systems suggested a higher incidence of blood dyscrasias (i.e., agranulocytosis, neutropenia and pancytopenia) in patients receiving mesalamine-containing products such as CANASA who were 65 years or older compared to younger patients. Monitor complete blood cell counts and platelet counts in elderly patients during treatment with CANASA. In general, consider the greater frequency of decreased hepatic, renal, or cardiac function, and of concurrent disease or other drug therapy in elderly patients when prescribing CANASA [see Use in Specific Populations (8.6)].

8.6 Renal Impairment

Mesalamine is known to be substantially excreted by the kidney, and the risk of adverse reactions may be greater in patients with impaired renal function. Evaluate renal function in all patients prior to initiation and periodically while on CANASA therapy. Monitor patients with known renal impairment or history of renal disease or taking nephrotoxic drugs for decreased renal function and mesalamine-related adverse reactions. Discontinue CANASA if renal function deteriorates while on therapy [see Warnings and Precautions (5.1), Adverse Reactions (6.2), Drug Interactions (7.1)].

10 OVERDOSAGE

Mesalamine absorption from the colon is limited; however, CANASA is an aminosalicylate, and symptoms of salicylate toxicity include nausea, vomiting and abdominal pain, tachypnea, hyperpnea, tinnitus, and neurologic symptoms (headache, dizziness, confusion, seizures). Severe salicylate intoxication may lead to electrolyte and blood pH imbalance and potentially to other organ (e.g., renal and liver) involvement. There is no specific antidote for mesalamine overdose. Correct fluid and electrolyte imbalance by the administration of appropriate intravenous therapy and maintain adequate renal function.

11 DESCRIPTION

The active ingredient in CANASA 1000 mg suppositories for rectal use is mesalamine, also known as mesalazine or 5-aminosalicylic acid (5-ASA). Chemically, mesalamine is 5-amino-2-hydroxybenzoic acid, and is classified as an aminosalicylate. Each CANASA rectal suppository contains 1000 mg of mesalamine (USP) in a base of Hard Fat, NF.

The empirical formula is C7H7NO3, representing a molecular weight of 153.14. The structural formula is:

12 CLINICAL PHARMACOLOGY

12.1 Mechanism of Action

The mechanism of action of mesalamine is not fully understood, but appears to be a topical anti-inflammatory effect on colonic epithelial cells. Mucosal production of arachidonic acid metabolites, both through the cyclooxygenase pathways, i.e., prostanoids, and through the lipoxygenase pathways, i.e., leukotrienes and hydroxyeicosatetraenoic acids, is increased in patients with ulcerative colitis, and it is possible that mesalamine diminishes inflammation by blocking cyclooxygenase and inhibiting prostaglandin production in the colon.

12.3 Pharmacokinetics

Absorption

Mesalamine (5-ASA) administered as a rectal suppository is variably absorbed. In patients with ulcerative colitis treated with mesalamine 500 mg rectal suppositories, administered once every eight hours for six days, the mean mesalamine peak plasma concentration (Cmax) was 353 ng/mL (CV=55%) following the initial dose and 361 ng/mL (CV=67%) at steady state. The mean minimum steady state plasma concentration (Cmin) was 89 ng/mL (CV=89%). Absorbed mesalamine does not accumulate in the plasma.

Distribution

Mesalamine administered as a rectal suppository distributes in rectal tissue to some extent.

Elimination

In patients with ulcerative proctitis treated with mesalamine 500 mg as a rectal suppository every 8 hours for 6 days, the mean elimination half-life was 5 hours (CV=73%) for 5-ASA and 5 hours (CV=63%) for N-acetyl-5-ASA, the active metabolite, following the initial dose. At steady state, the mean elimination half-life was 7 hours for both 5-ASA and N-acetyl-5-ASA (CV=102% for 5-ASA and 82% for N-acetyl-5-ASA).

Metabolism

The absorbed mesalamine is extensively metabolized, mainly to N-acetyl-5-ASA in the liver and in the gut mucosal wall. In patients with ulcerative colitis treated with one mesalamine 500 mg rectal suppository every eight hours for six days, the peak concentration (Cmax) of N-acetyl-5-ASA ranged from 467 ng/mL to 1399 ng/mL following the initial dose and from 193 ng/mL to 1304 ng/mL at steady state.

Excretion

Mesalamine is eliminated from plasma mainly by urinary excretion, predominantly as N-acetyl-5-ASA. In patients with ulcerative proctitis treated with mesalamine 500 mg as a rectal suppository every 8 hours for 6 days, 12% or less of the dose was eliminated in urine as unchanged 5-ASA and 8% to 77% was eliminated as N-acetyl-5-ASA following the initial dose. At steady state, 11% or less of the dose was eliminated in the urine as unchanged 5-ASA and 3% to 35% was eliminated as N-acetyl-5-ASA.

13 NONCLINICAL TOXICOLOGY

13.1 Carcinogenesis, Mutagenesis, Impairment of Fertility

Mesalamine caused no increase in the incidence of neoplastic lesions over controls in a two-year study of Wistar rats fed up to 320 mg/kg/day of mesalamine admixed with diet (about 1.7 times the recommended human intra-rectal dose of CANASA, based on body surface area).

Mesalamine was not mutagenic in the Ames test, the mouse lymphoma cell (TK+/-) forward mutation test, or the mouse micronucleus test.

No effects on fertility or reproductive performance of the male and female rats were observed at oral mesalamine doses up to 320 mg/kg/day (about 1.7 times the recommended human intra-rectal dose of CANASA, based on body surface area).

13.2 Animal Toxicology and/or Pharmacology

Toxicology studies of mesalamine were conducted in rats, mice, rabbits and dogs, and the kidney was the main target organ of toxicity. In rats, adverse renal effects were observed at a single oral dose of 600 mg/kg (about 3.2 times the recommended human intra-rectal dose of CANASA, based on body surface area) and at intravenous doses of >214 mg/kg (about 1.2 times the recommended human intra-rectal dose of CANASA, based on body surface area). In a 13-week oral gavage toxicity study in rats, papillary necrosis and/or multifocal tubular injury were observed in males receiving 160 mg/kg (about 0.86 times the recommended human intra-rectal dose of CANASA, based on body surface area) and in both males and females at 640 mg/kg (about 3.5 times the recommended human intra-rectal dose of CANASA, based on body surface area). In a combined 52-week toxicity and 127-week carcinogenicity study in rats, degeneration of the kidneys and hyalinization of basement membranes and Bowman’s capsule were observed at oral doses of 100 mg/kg/day (about 0.54 times the recommended human intra-rectal dose of CANASA, based on body surface area) and above. In a 14-day rectal toxicity study of mesalamine suppositories in rabbits, intra-rectal doses up to 800 mg/kg (about 8.6 times the recommended human intra-rectal dose of CANASA, based on body surface area) was not associated with any adverse effects. In a six-month oral toxicity study in dogs, doses of 80 mg/kg (about 1.4 times the recommended human intra-rectal dose of CANASA, based on body surface area) and higher caused renal pathology similar to that described for the rat. In a rectal toxicity study of mesalamine suppositories in dogs, a dose of 166.6 mg/kg (about 3 times the recommended human intra-rectal dose of CANASA, based on body surface area) produced chronic nephritis and pyelitis. In the 12-month eye toxicity study in dogs, keratoconjunctivitis sicca (KCS) occurred at oral doses of 40 mg/kg (about 0.72 times the recommended human intra-rectal dose of CANASA, based on body surface area) and above.

14 CLINICAL STUDIES

Two double-blind, placebo-controlled, multicenter trials of mesalamine suppositories were conducted in North America in adult patients with mildly to moderately active ulcerative proctitis. The regimen in Study 1 was a 500 mg mesalamine suppository administered rectally three times daily and in Study 2 was a 500 mg mesalamine suppository administered rectally twice daily. In both trials, patients had an average extent of proctitis (upper disease boundary) of approximately 10 cm and approximately 80% of patients had multiple prior episodes of proctitis. A total of 173 patients were evaluated (Study 1, N=79; Study 2, N=94), of which 89 patients received mesalamine, and 84 patients received placebo. The mean age of patients was 39 years (range 17 to 73 years), 60% were female, and 97% were white.

The primary measures of efficacy were clinical disease activity index (DAI) and histologic evaluations in both trials. The DAI is a composite index reflecting rectal bleeding, stool frequency, mucosal appearance at endoscopy, and a physician’s global assessment of disease. Patients were evaluated clinically and sigmoidoscopically after 3 and 6 weeks of treatment.

Compared to placebo, mesalamine suppositories were statistically (p<0.01) superior to placebo in both trials with respect to improvement in stool frequency, rectal bleeding, mucosal appearance, disease severity, and overall disease activity after 3 and 6 weeks of treatment. The effectiveness of mesalamine suppositories was statistically significant irrespective of sex, extent of proctitis, duration of current episode, or duration of disease.

An additional multicenter, open-label, randomized, parallel group study in 99 patients diagnosed with mildly to moderately ulcerative proctitis compared 1000 mg CANASA administered rectally once daily at bedtime (N=35) to 500 mg mesalamine suppository administered rectally twice daily, in the morning and at bedtime (N=46), for 6 weeks.

The primary measures of efficacy included the clinical disease activity index (DAI) and histologic evaluations. Patients were evaluated clinically and sigmoidoscopically at 3 and 6 weeks of treatment.

The efficacy at 6 weeks was not different between the treatment groups. Both were effective in the treatment of ulcerative proctitis and resulted in a significant decrease at 6 weeks in DAI: in the mesalamine 500 mg twice daily group, the mean DAI value decreased from 6.6 to 1.6, and in the 1000 mg at bedtime group, the mean DAI value decreased from 6.2 to 1.3, which represents a decrease of greater than 75% in both groups. After 6 weeks of treatment, a DAI score of less than 3 was achieved in 78% of patients in the mesalamine 500 mg twice daily group and 86% of patients in the CANASA 1000 mg once daily group. The recommended dosage of CANASA is 1000 mg administered rectally once daily at bedtime [see Dosage and Administration (2)].

16 HOW SUPPLIED/STORAGE AND HANDLING

CANASA 1000 mg suppositories for rectal administration are available as bullet shaped, light tan to grey suppositories containing 1000 mg mesalamine supplied in boxes of 30 and 42 individually plastic wrapped suppositories (NDC 58914-501-56 and 58914-501-42).

Store below 25ºC (77ºF), may be refrigerated. Keep away from direct heat, light or humidity.

17 PATIENT COUNSELING INFORMATION

Advise patients to read the FDA-approved patient labeling (Patient Information)

Administration [see Dosage and Administration (2)]

Advise patients:

- Do not cut or break the suppository.
- Retain the suppository for one to three hours or longer, if possible.
- Drink an adequate amount of fluids.
- If a dose of CANASA is missed, administer as soon as possible, unless it is almost time for next dose. Do not use two CANASA suppositories at the same time to make up for a missed dose.
- Urine may become discolored reddish-brown while taking CANASA when it comes in contact with surfaces or water treated with hypochlorite-containing bleach. If discolored urine is observed, advise patients to observe their urine flow. Report to the healthcare provider only if urine is discolored on leaving the body, before contact with any surface or water (e.g., in the toilet).
- CANASA suppositories will cause staining of direct contact surfaces, including but not limited to fabrics, flooring, painted surfaces, marble, granite, vinyl, and enamel. Keep CANASA away from these surfaces to prevent staining.

Renal Impairment

- Inform patients that CANASA may decrease their renal function, especially if they have known renal impairment or are taking nephrotoxic drugs, including NSAIDs, and periodic monitoring of renal function will be performed while they are on therapy. Advise patients to complete all blood tests ordered by their healthcare provider [see Warnings and Precautions (5.1), Drug Interactions (7.1)].

Mesalamine-Induced Acute Intolerance Syndrome and Other Hypersensitivity Reactions

- Inform patients of the signs and symptoms of hypersensitivity reactions. Instruct patients to stop taking CANASA and report to their healthcare provider if they experience new or worsening symptoms Acute Intolerance Syndrome (cramping, abdominal pain, bloody diarrhea, fever, headache, malaise, conjunctivitis and rash) or other symptoms suggestive of mesalamine-induced hypersensitivity [see Warnings and Precautions (5.2, 5.3)].

Hepatic Failure

- Inform patients with known liver disease of the signs and symptoms of worsening liver function and advise them to report to their healthcare provider if they experience such signs or symptoms [see Warnings and Precautions (5.4)].

Severe Cutaneous Adverse Reactions

- Inform patients of the signs and symptoms of severe cutaneous adverse reactions. Instruct patients to stop taking CANASA and report to their healthcare provider at first appearance of a severe cutaneous adverse reaction or any other sign of hypersensitivity [see Warnings and Precautions (5.5)].

Photosensitivity

- Advise patients with pre-existing skin conditions to avoid sun exposure, wear protective clothing, and use a broad-spectrum sunscreen when outdoors [see Warnings and Precautions (5.6)].

Nephrolithiasis

- Instruct patients to drink an adequate amount of fluids during treatment in order to minimize the risk of kidney stone formation and to contact their healthcare provider if they experience signs or symptoms of a kidney stone (e.g., severe side or back pain, blood in the urine) [see Warnings and Precautions (5.7)].

Blood Disorders

- Inform elderly patients and those taking azathioprine or 6-mercaptopurine of the risk for blood disorders and the need for periodic monitoring of complete blood cell counts and platelet counts while on therapy. Advise patients to complete all blood tests ordered by their healthcare provider [see Drug Interactions (7.2), Use in Specific Populations (8.5)].

Distributed by:
AbbVie Inc.
North Chicago, IL 60064

© 2024 AbbVie. All rights reserved.
CANASA and its design are trademarks of Aptalis Pharma Canada ULC, an AbbVie company.

V5.1USPI0501

PATIENT INFORMATION
CANASA (Kay-nay-suh)
(mesalamine)
suppositories, for rectal use

What is CANASA?
CANASA is a prescription medicine used to treat adults with active ulcerative proctitis (ulcerative rectal colitis).
It is not known if CANASA is safe and effective in children.

Do not use CANASA if you are:

- allergic to medicines that contain salicylates, including aspirin.
- allergic to mesalamine or any of the ingredients in CANASA. See the end of this Patient Information leaflet for a complete list of ingredients in CANASA.

Ask your doctor if you are not sure if your medicine is listed above.

Before using CANASA, tell your doctor if you have any medical conditions, including if you:

- have a history of allergic reaction to the medicine sulfasalazine (Azulfidine).
- have kidney problems.
- have ever had inflammation of the sac around your heart (pericarditis).
- have liver problems.
- are pregnant or plan to become pregnant. It is not known if CANASA can harm your unborn baby.
- are breastfeeding or plan to breastfeed. CANASA can pass into your breast milk. Talk to your doctor about the best way to feed your baby if you use CANASA.

Tell your doctor about all the medicines you take, including prescription and over-the-counter medicines, vitamins and herbal supplements.
Using CANASA with certain other medicines may affect each other. Using CANASA with other medicines can cause serious side effects.
Especially tell your doctor if you take nonsteroidal anti-inflammatory drugs (NSAIDS), or medicines that contain azathioprine or 6-mercaptopurine. Taking CANASA with NSAIDS may cause kidney problems. Taking CANASA with azathioprine or 6-mercaptopurine may cause blood problems. Ask your doctor if you are not sure if you are taking one of these medicines.
Your doctor may do certain tests during treatment with CANASA.
Know the medicines you take. Keep a list of them to show your doctor and pharmacist when you get a new medicine.

How should I take CANASA?

- Use CANASA exactly as prescribed by your doctor. Your doctor will tell you how long to continue using CANASA.
- CANASA comes as a suppository that you insert into your rectum.
- Do not cut or break the suppository.
- Use CANASA 1 time each day at bedtime, for 3 to 6 weeks. It is not known if CANASA is safe and effective for use for longer than 6 weeks.
- After you insert CANASA in your rectum, try to keep (retain) the suppository in your rectum for 1 to 3 hours or longer if possible.
- It is important for you to stay well hydrated during treatment with CANASA. Be sure to drink plenty of fluids while taking CANASA.
- If you miss a dose of CANASA, insert it as soon as you remember. If it is almost time for your next dose, skip the missed dose. Insert the next dose at your regular time. Do not insert 2 doses at the same time.
- CANASA can stain surfaces including clothing and other fabrics, flooring, painted surfaces, marble, granite, vinyl and enamel. Keep CANASA away from these surfaces to prevent staining.

What are the possible side effects of CANASA?
CANASA may cause serious side effects, including:

- kidney problems. Your doctor will do certain tests before you start using CANASA and during your treatment with CANASA.

- acute intolerance syndrome and other allergic reactions. Some people who use CANASA can have allergic type reactions, including Acute Intolerance Syndrome. Other allergic reactions can cause heart problems including an inflammation of the sac around the heart (pericarditis), blood problems, and problems with other organs in the body including the kidneys, liver and lungs. These problems usually happen in people who have had an allergic reaction to medicines containing sulfasalazine. Stop using CANASA and tell your doctor right away if you get any of these symptoms:

○ cramps

○ fever

○ stomach (abdominal) pain

○ headache

○ bloody diarrhea

○ rash

○ chest pain

○ shortness of breath

○ decrease in the amount of urine

○ fatigue

○ eye inflammation

- liver problems. This can happen in people who have a history of liver problems and have taken other medicines that contain mesalamine. Tell your doctor right away if you get any of these symptoms while using CANASA:

○ yellowing of your eyes

○ flu-like symptoms

○ itchy skin

○ nausea or vomiting

○ feeling very tired

- serious skin reactions. Some people who use CANASA can have severe skin reactions. Stop using CANASA and tell your doctor right away if you develop any of the following signs or symptoms of a severe skin reaction, including:

○ blisters or peeling of your skin
○ mouth sores
○ blisters on your lips, or around your mouth or eyes

○ high fever or flu-like symptoms
○ enlarged lymph nodes
○ skin rash

- sun sensitivity. CANASA can make your skin sensitive to the sun if you have skin conditions such as atopic dermatitis and atopic eczema. Try to limit your time in the sun. You should use sunscreen and wear a hat and clothes that cover your skin if you have to be in the sunlight.

- kidney stones. Drink plenty of fluids when using CANASA to decrease your chance of getting kidney stones. Call your doctor right away if you get any of these symptoms:

○ severe pain in your side
○ severe pain in your back

○ blood in your urine

The most common side effects of CANASA include:

○ dizziness

○ rectal pain

○ acne

○ fever

○ inflammation of the large intestine (colitis)

○ rash

These are not all of the possible side effects of CANASA.
Call your doctor for medical advice about side effects. You may report side effects to FDA at 1-800-FDA-1088.

How should I store CANASA?

- Store CANASA at room temperature between 68°F to 77°F (20°C to 25°C).
- CANASA may be refrigerated.
- Keep CANASA away from direct heat, light, or humidity.

Keep CANASA and all medicines out of the reach of children.

General information about the safe and effective use of CANASA.
Medicines are sometimes prescribed for purposes other than those listed in a Patient Information leaflet. Do not use CANASA for a condition for which it was not prescribed. Do not give CANASA to other people, even if they have the same symptoms that you have. It may harm them.
Urine may become discolored reddish-brown while taking CANASA when it comes in contact with surfaces or water treated with hypochlorite-containing bleach.
You can ask your pharmacist or healthcare provider for information about CANASA that is written for health professionals.

What are the ingredients in CANASA?
Active ingredients: mesalamine
Inactive ingredients: hard fat base
Distributed by: AbbVie Inc. North Chicago, IL 60064
© 2024 AbbVie. All rights reserved. CANASA and its design are trademarks of Aptalis Pharma Canada ULC, an AbbVie company.

This Patient Information has been approved by the U.S. Food and Drug Administration. Revised: September 2024

V4.1PPI501

PRINCIPAL DISPLAY PANEL

NDC 58914-501-33
3 Rectal Suppositories
Canasa
(mesalamine) suppositories
for rectal use 1000 mg
Rx Only

PRINCIPAL DISPLAY PANEL

NDC 58914-501-56
30 Rectal Suppositories
Canasa
(mesalamine) suppositories
for rectal use 1000 mg
For Rectal Use Only
Rx Only